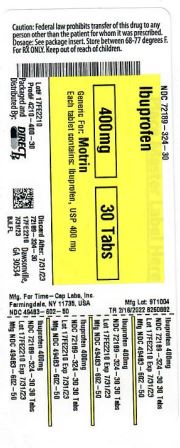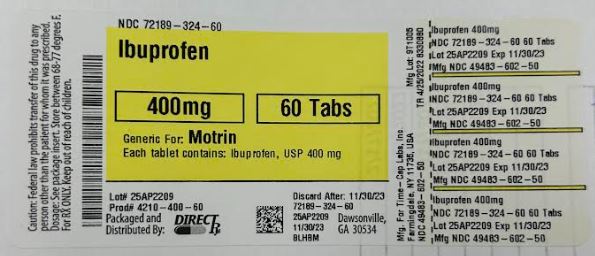 DRUG LABEL: IBUPROFEN
NDC: 72189-324 | Form: TABLET, FILM COATED
Manufacturer: Direct Rx
Category: prescription | Type: HUMAN PRESCRIPTION DRUG LABEL
Date: 20250121

ACTIVE INGREDIENTS: IBUPROFEN 400 mg/1 1
INACTIVE INGREDIENTS: TITANIUM DIOXIDE; CROSCARMELLOSE SODIUM; POLYETHYLENE GLYCOL, UNSPECIFIED; POLYVINYL ALCOHOL, UNSPECIFIED; TALC; MAGNESIUM STEARATE; SILICON DIOXIDE; CELLULOSE, MICROCRYSTALLINE; STARCH, CORN

Ibuprofen

HOW SUPPLIED

400mg (white to of white, round, biconvex, film coated tablets debossed with '121' on one side and plain on the other side) Bottles of 100 & 500

600mg (white to off white, capsule shaped, biconvex, film coated tablets debossed with '122' on one side and plain on the other side) Bottles of 30, 50, 100 & 500

800 mg (white to off-white, capsule shaped, biconvex, film-coated tablets debossed with ‘123’ on one side and plain on other side)